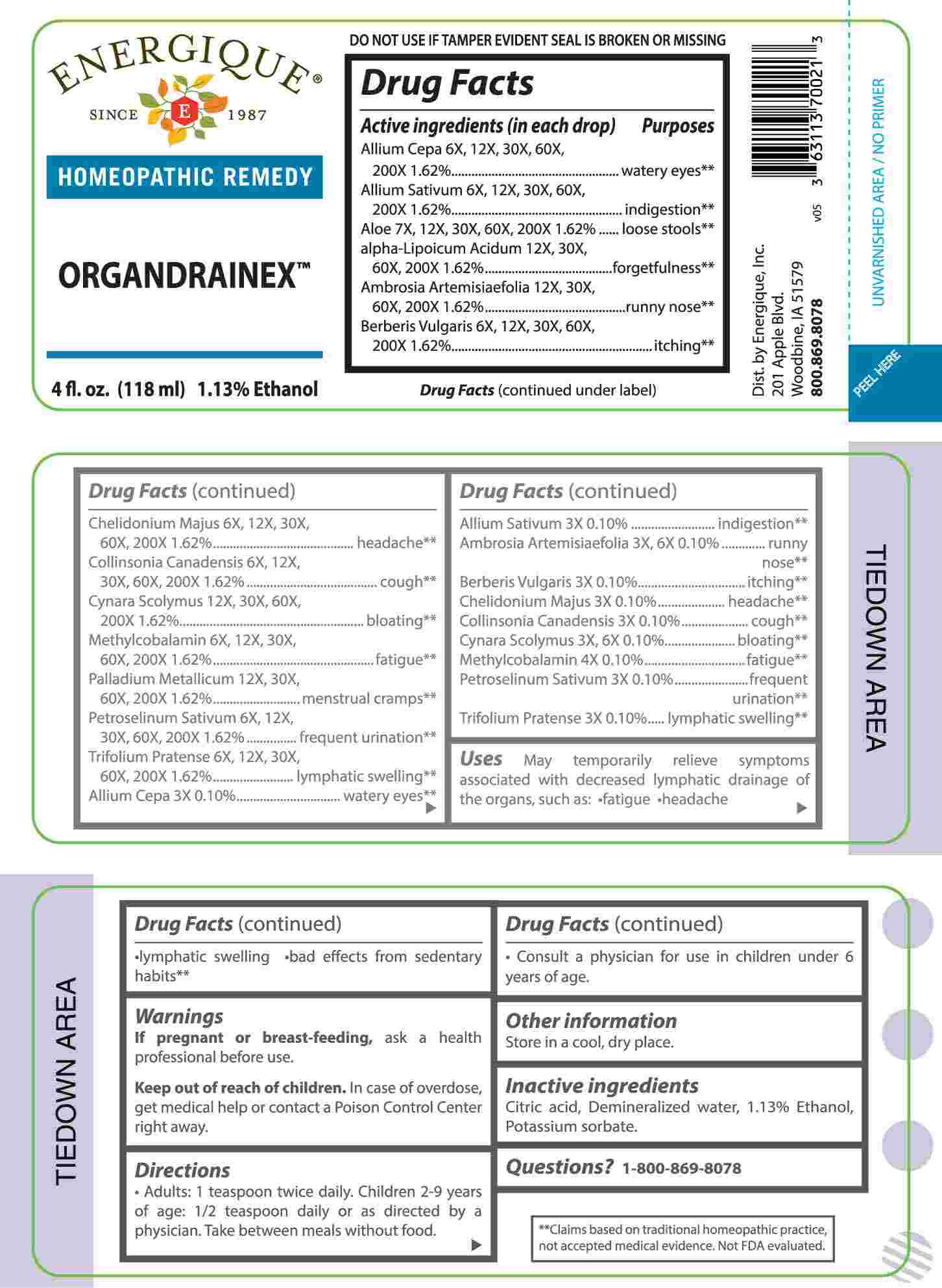 DRUG LABEL: Organdrainex
NDC: 44911-0660 | Form: LIQUID
Manufacturer: Energique, Inc.
Category: homeopathic | Type: HUMAN OTC DRUG LABEL
Date: 20250128

ACTIVE INGREDIENTS: ONION 3 [hp_X]/1 mL; GARLIC 3 [hp_X]/1 mL; AMBROSIA ARTEMISIIFOLIA WHOLE 3 [hp_X]/1 mL; BERBERIS VULGARIS ROOT BARK 3 [hp_X]/1 mL; CHELIDONIUM MAJUS WHOLE 3 [hp_X]/1 mL; COLLINSONIA CANADENSIS ROOT 3 [hp_X]/1 mL; CYNARA SCOLYMUS LEAF 3 [hp_X]/1 mL; PETROSELINUM CRISPUM WHOLE 3 [hp_X]/1 mL; TRIFOLIUM PRATENSE FLOWER 3 [hp_X]/1 mL; METHYLCOBALAMIN 4 [hp_X]/1 mL; ALOE 7 [hp_X]/1 mL; ALPHA LIPOIC ACID 12 [hp_X]/1 mL; PALLADIUM 12 [hp_X]/1 mL
INACTIVE INGREDIENTS: ANHYDROUS CITRIC ACID; POTASSIUM SORBATE; WATER; ALCOHOL

DRUG FACTS:

ACTIVE INGREDIENTS:

(in each drop) Allium Cepa 6X, 12X, 30X, 60X, 200X 1.62%, Allium Sativum 6X, 12X, 30X, 60X, 200X 1.62%, Aloe 7X, 12X, 30X, 60X, 200X 1.62%, Alpha-Lipoicum Acidum 12X, 30X, 60X, 200X 1.62%, Ambrosia Artemisiaefolia 12X, 30X, 60X, 200X 1.62%, Berberis Vulgaris 6X, 12X, 30X, 60X, 200X 1.62%, Chelidonium Majus 6X, 12X, 30X, 60X, 200X 1.62%, Collinsonia Canadensis 6X, 12X, 30X, 60X, 200X 1.62%, Cynara Scolymus 12X, 30X, 60X, 200X 1.62%, Methylcobalamin 6X, 12X, 30X, 60X, 200X 1.62%, Palladium Metallicum 12X, 30X, 60X, 200X 1.62%, Petroselinum Sativum 6X, 12X, 30X, 60X, 200X 1.62%, Trifolium Pratense 6X, 12X, 30X, 60X, 200X 1.62%, Allium Cepa 3X 0.10%, Allium Sativum 3X 0.10%, Ambrosia Artemisiaefolia 3X, 6X 0.10%, Berberis Vulgaris 3X 0.10%, Chelidonium Majus 3X 0.10%, Collinsonia Canadensis 3X 0.10%, Cynara Scolymus 3X, 6X 0.10%, Methylcobalamin 4X 0.10%, Petroselinum Sativum 3X 0.10%, Trifolium Pratense 3X 0.10%.

PURPOSE:

Allium Cepa – watery eyes,** Allium Sativum - indigestion,** Aloe – loose stools,** Alpha-Lipoicum Acidum - forgetfulness,** Ambrosia Artemisiaefolia – runny nose,** Berberis Vulgaris - itching,** Chelidonium Majus - headache,** Collinsonia Canadensis - cough,** Cynara Scolymus - bloating,** Methylcobalamin - fatigue,** Palladium Metallicum – menstrual cramps,** Petroselinum Sativum – frequent urination,** Trifolium Pratense – lymphatic swelling,** Allium Cepa – watery eyes,** Allium Sativum - indigestion,** Ambrosia Artemisiaefolia – runny nose,** Berberis Vulgaris - itching,** Chelidonium Majus - headache,** Collinsonia Canadensis - cough,** Cynara Scolymus - bloating,** Methylcobalamin - fatigue,** Petroselinum Sativum – frequent urination,** Trifolium Pratense – lymphatic swelling**

**Claims based on traditional homeopathic practice, not accepted medical evidence. Not FDA evaluated.

USES:

May temporarily relieve symptoms associated with decreased lymphatic drainage of the organs, such as:

•fatigue •headache •lymphatic swelling •bad effects from sedentary habits.**

**Claims based on traditional homeopathic practice, not accepted medical evidence. Not FDA evaluated.

WARNINGS:

If pregnant or breast-feeding, ask a health professional before use.

Keep out of reach of children. In case of overdose, get medical help or contact a Poison Control Center right away.

DO NOT USE IF TAMPER EVIDENT SEAL IS BROKEN OR MISSING

Store in a cool, dry place.

KEEP OUT OF REACH OF CHILDREN:

In case of overdose, get medical help or contact a Poison Control Center right away.

DIRECTIONS:

• Adults: 1 teaspoon twice daily. Children 2-9 years of age: 1/2 teaspoon daily, or as directed by a physician. Take between meals without food.

• Consult a physician for use in children under 6 years of age.

INACTIVE INGREDIENTS:

Citric acid, Demineralized water, 1.13% Ethanol, Potassium sorbate.

QUESTIONS:

Dist. by Energique, Inc.
201 Apple Blvd.
Woodbine, IA 51579

800.869.8078

PACKAGE LABEL DISPLAY:

ENERGIQUE

SINCE 1987

HOMEOPATHIC REMEDY

ORGANDRAINEX

4 fl. oz. (118 ml)